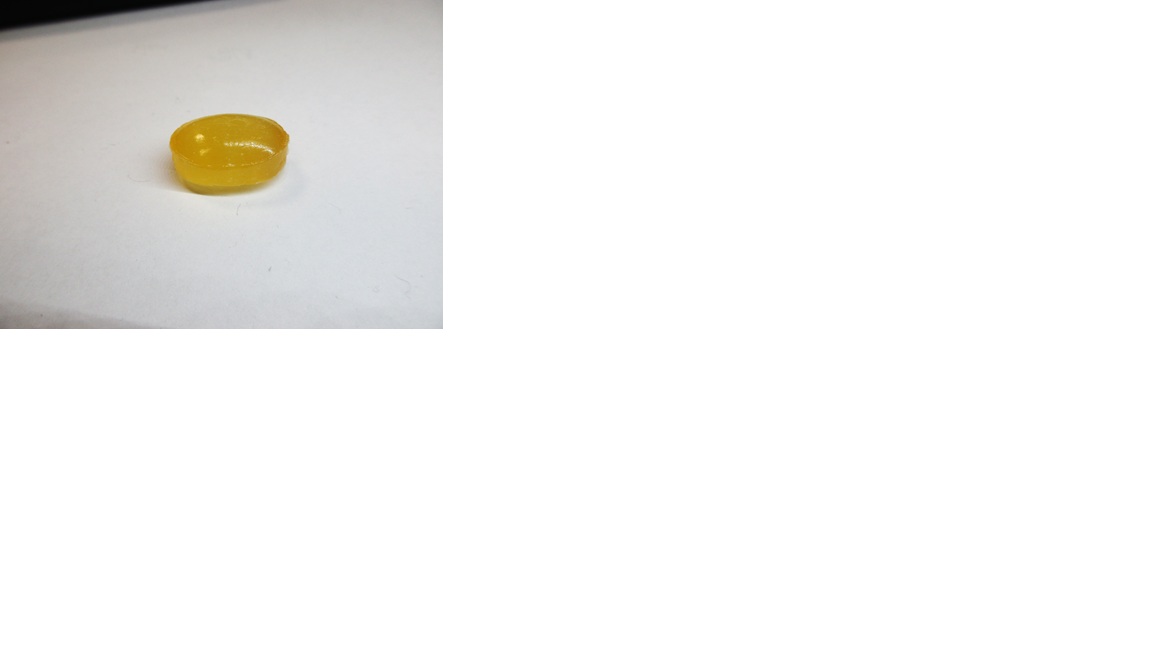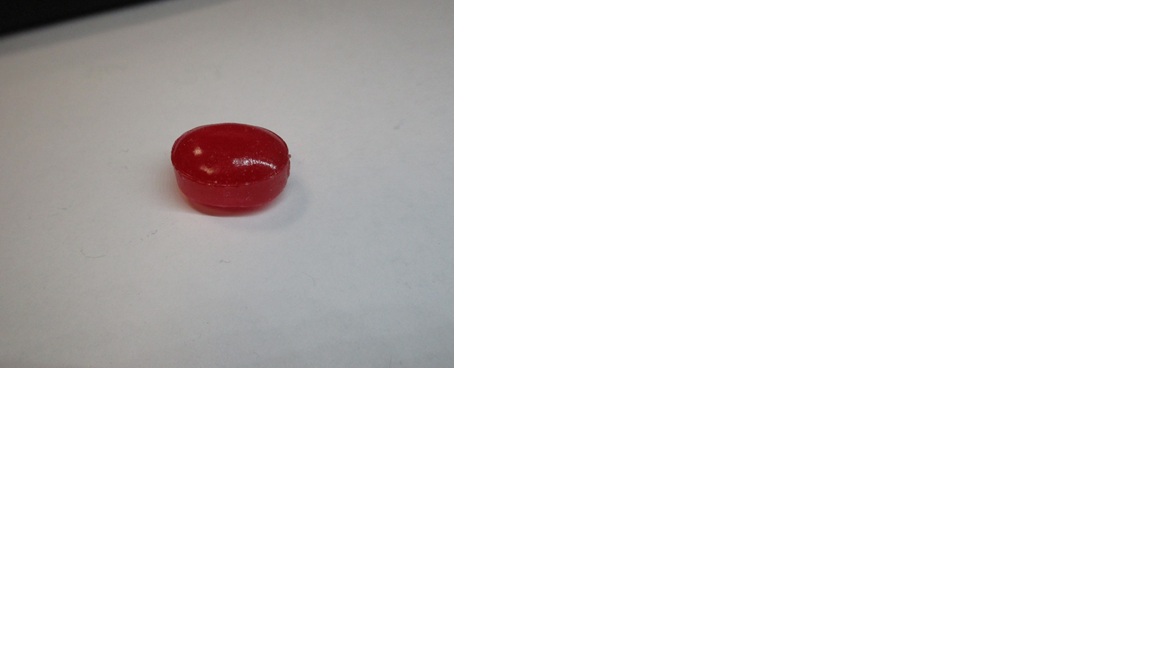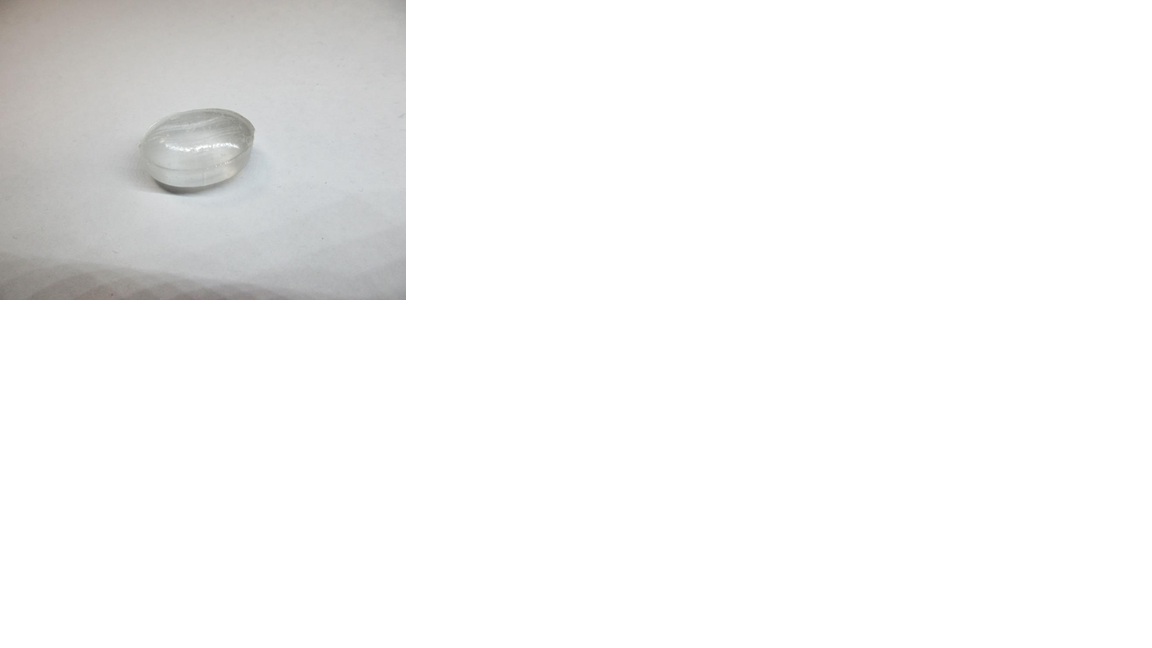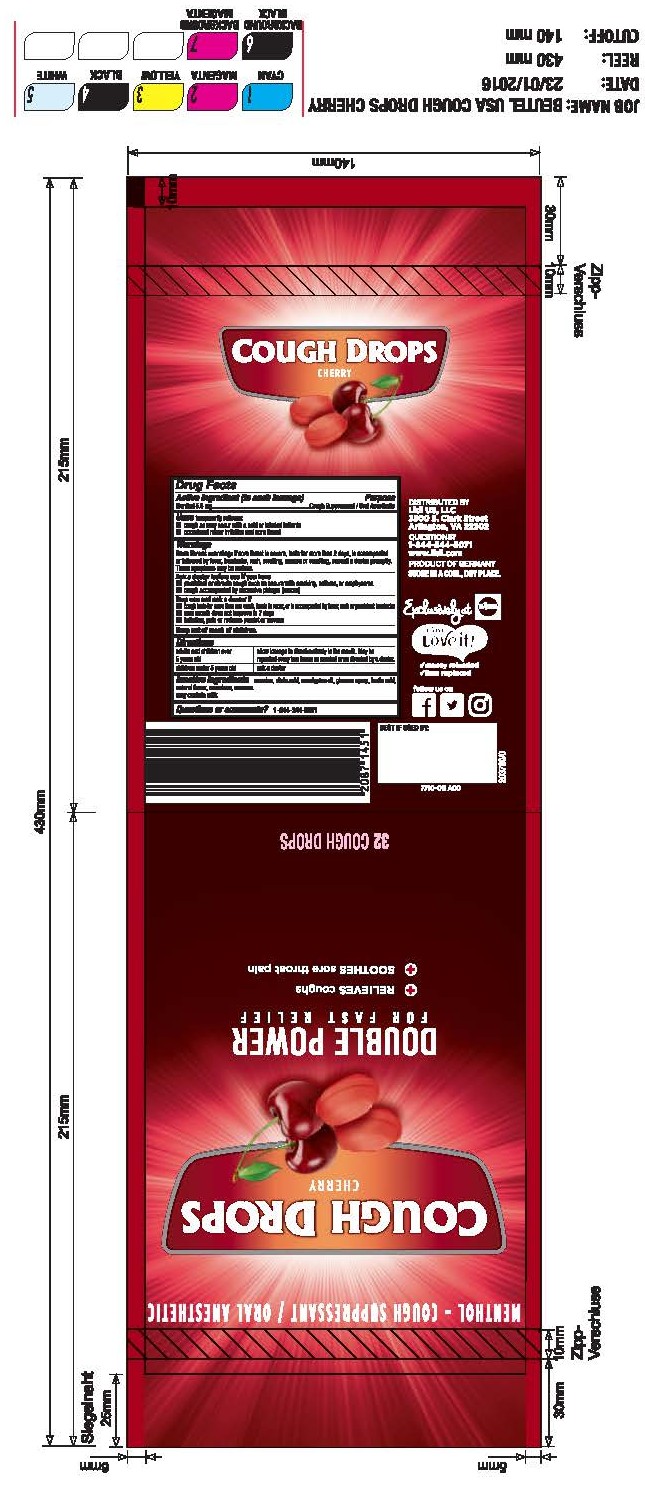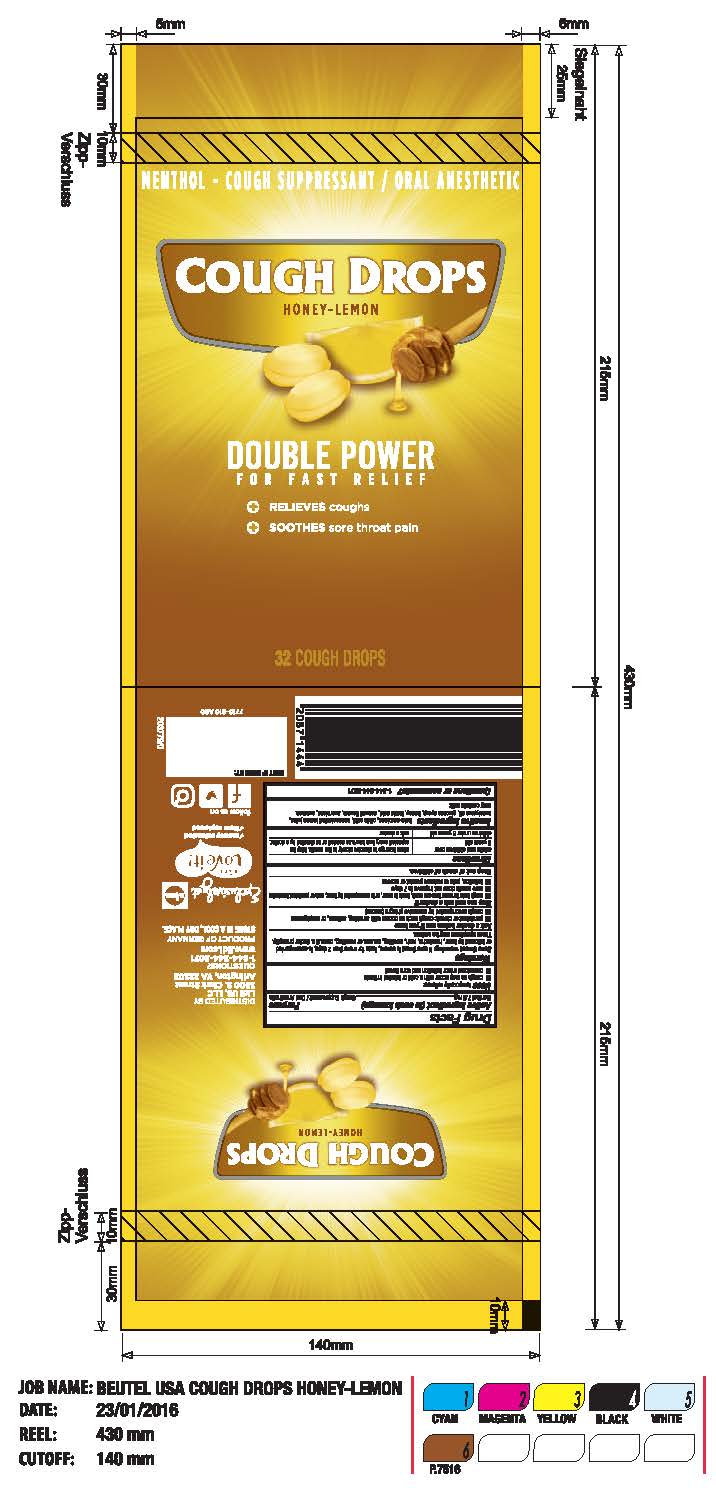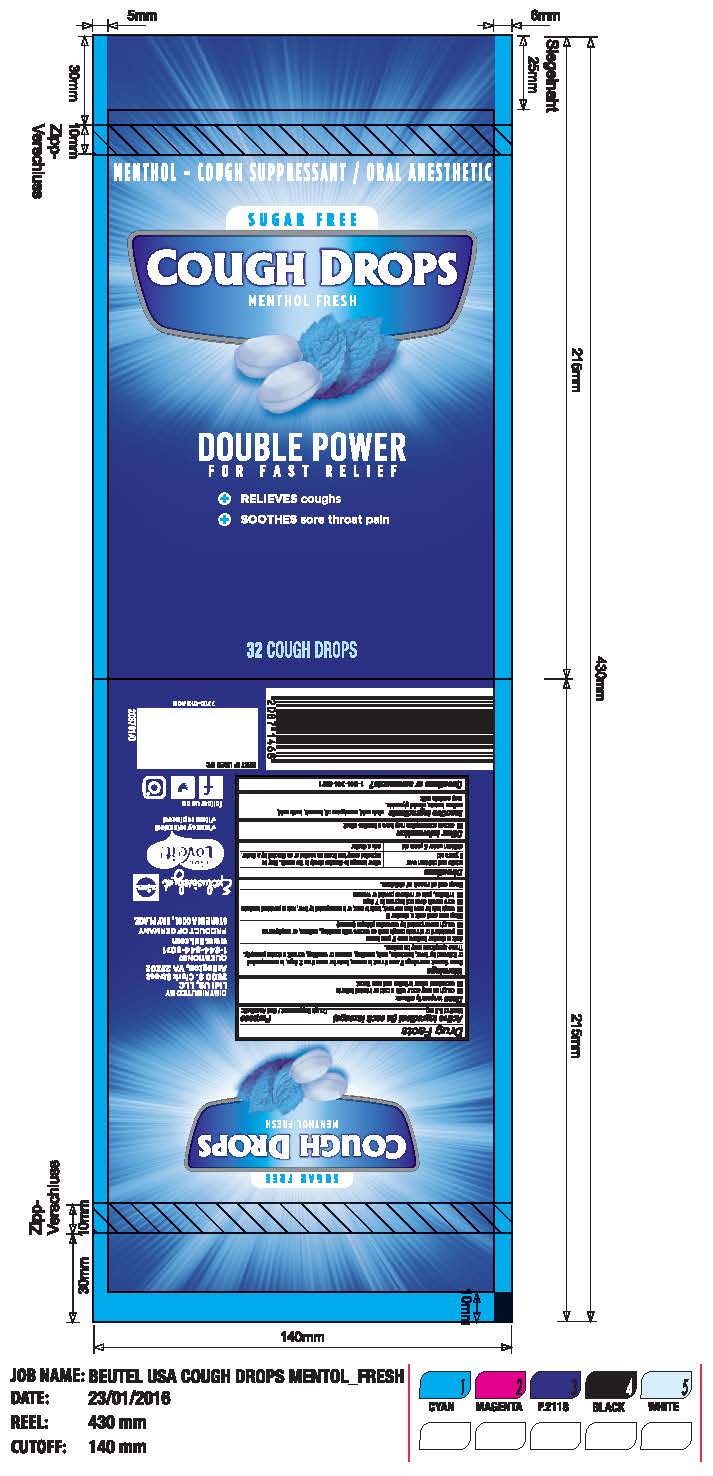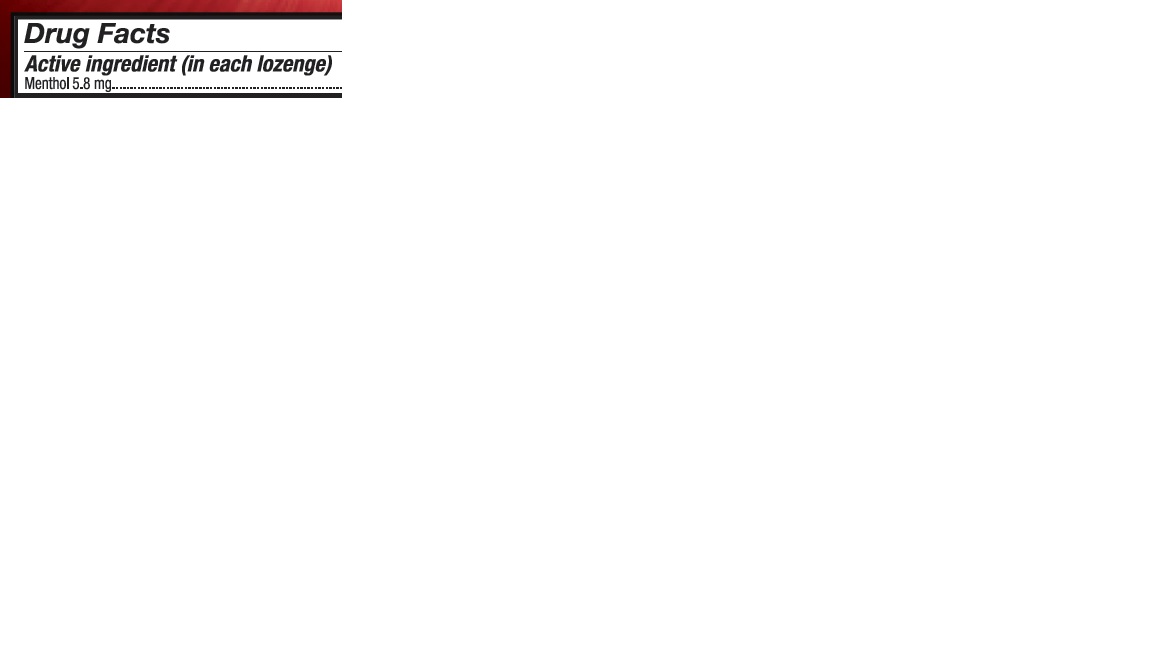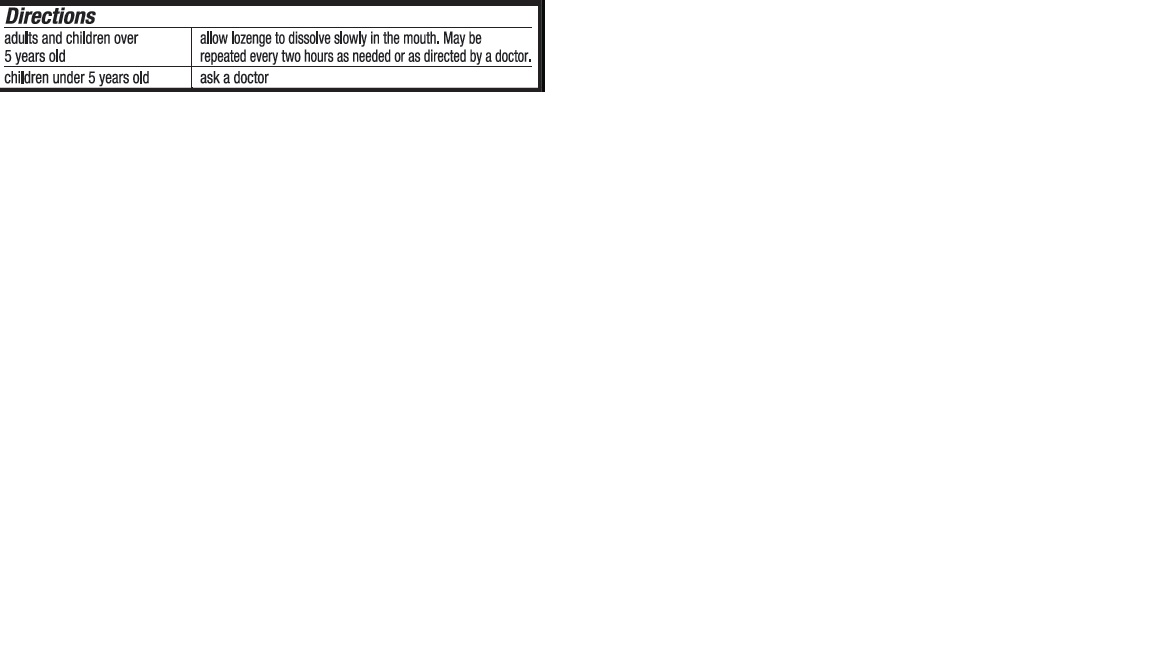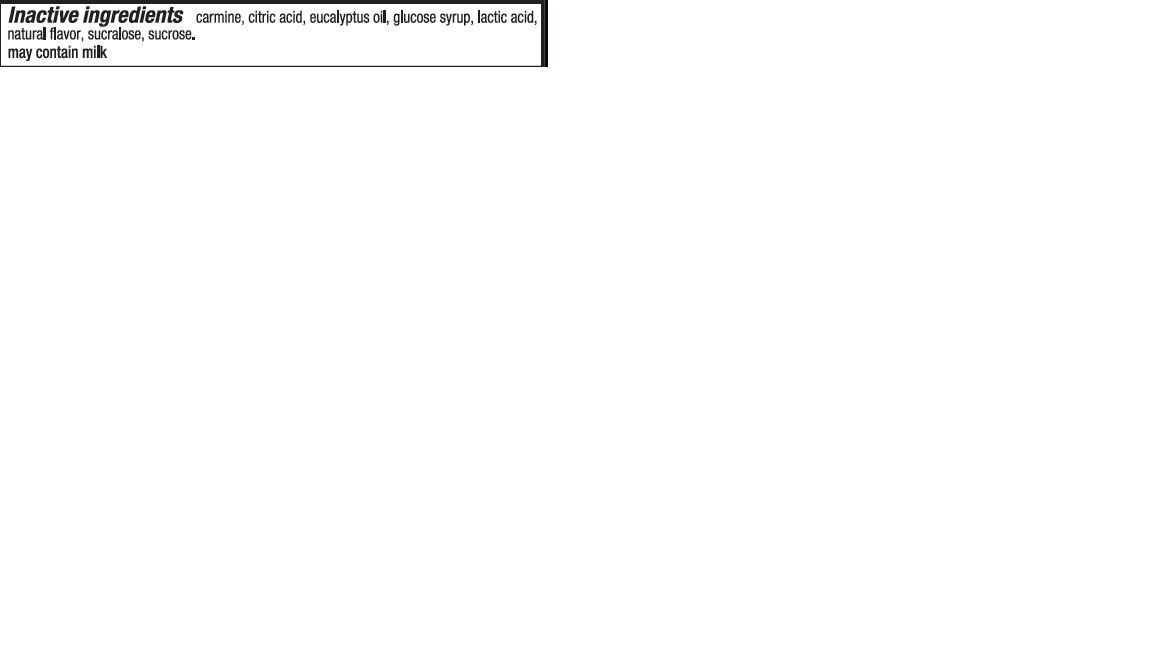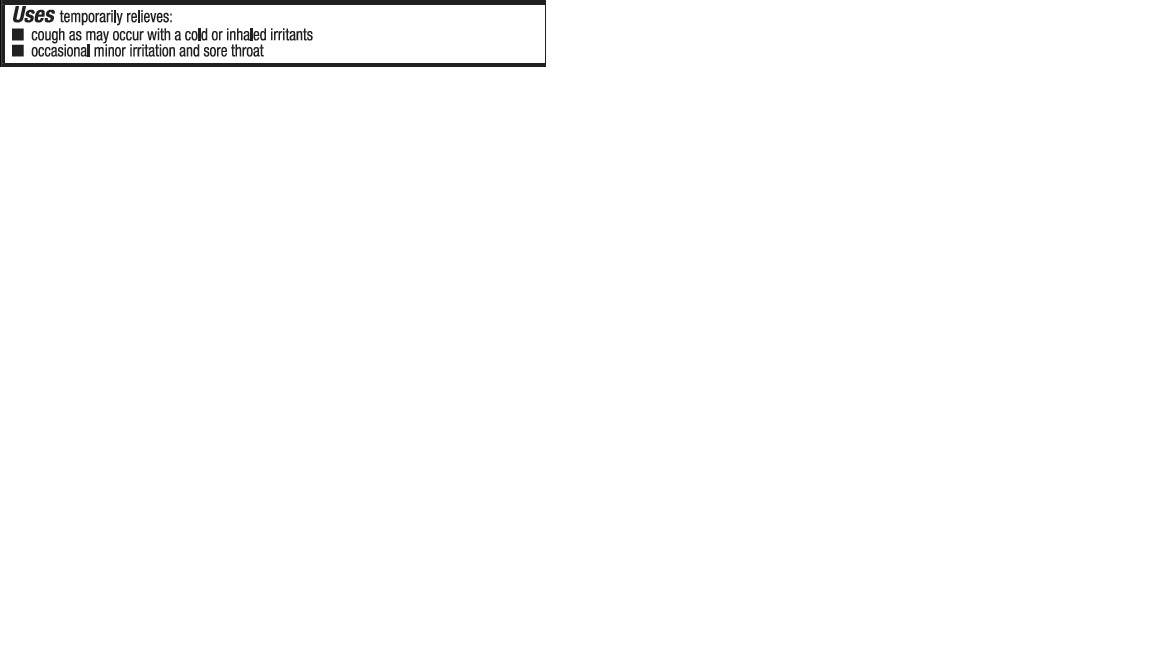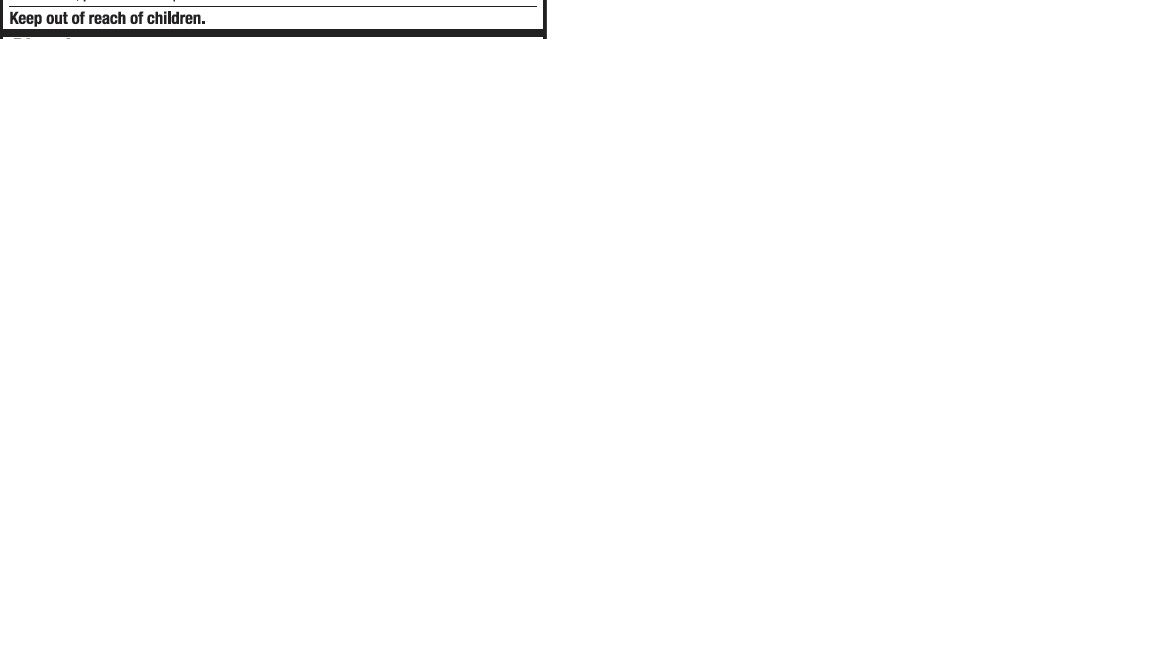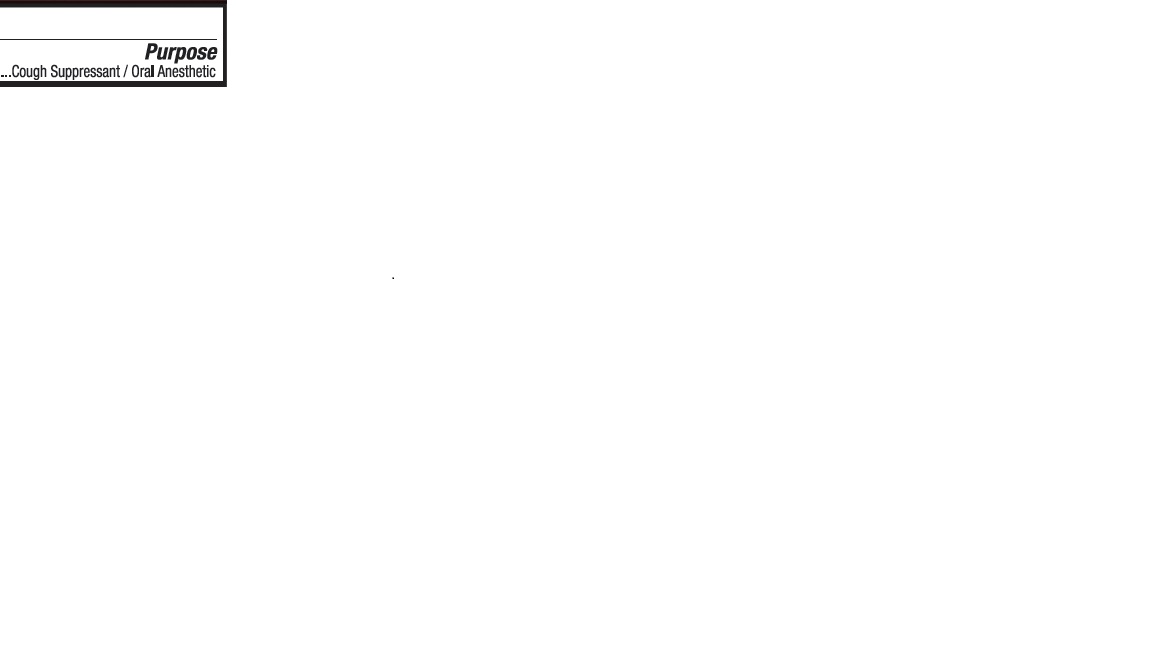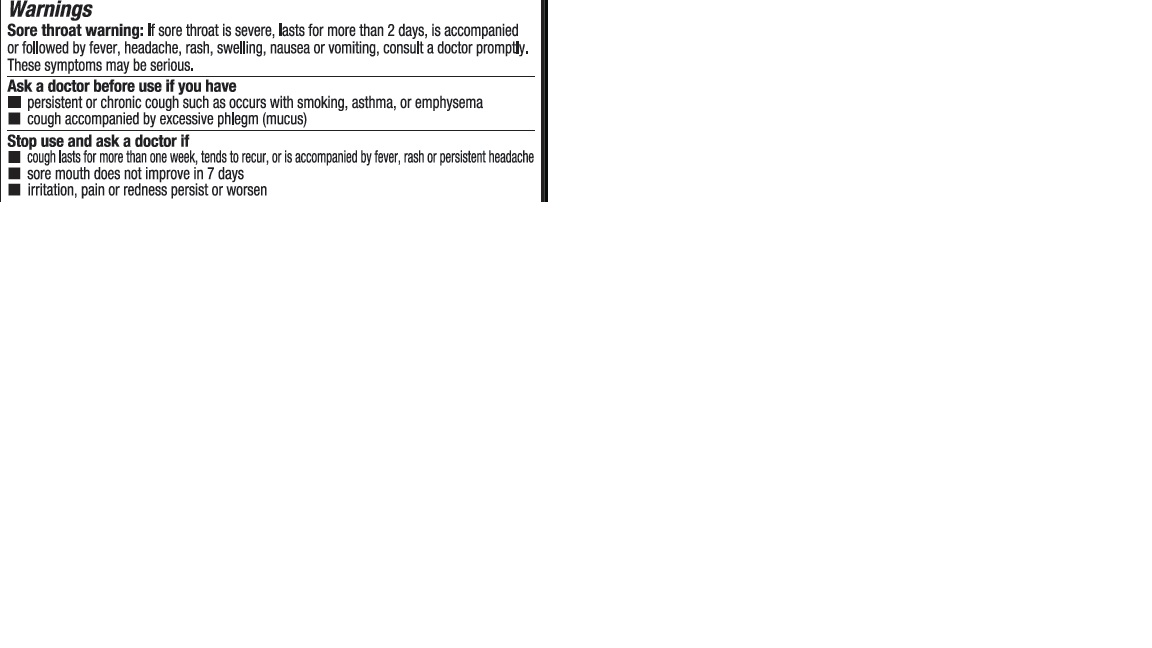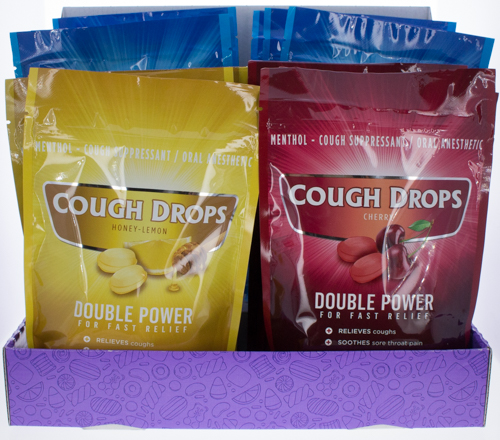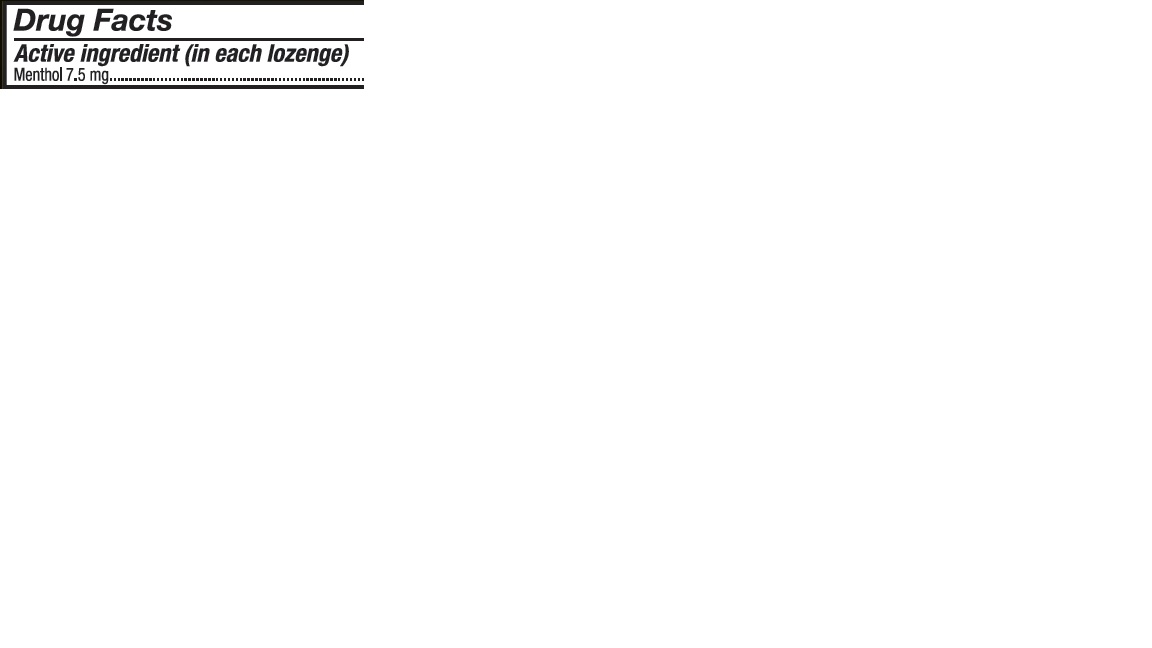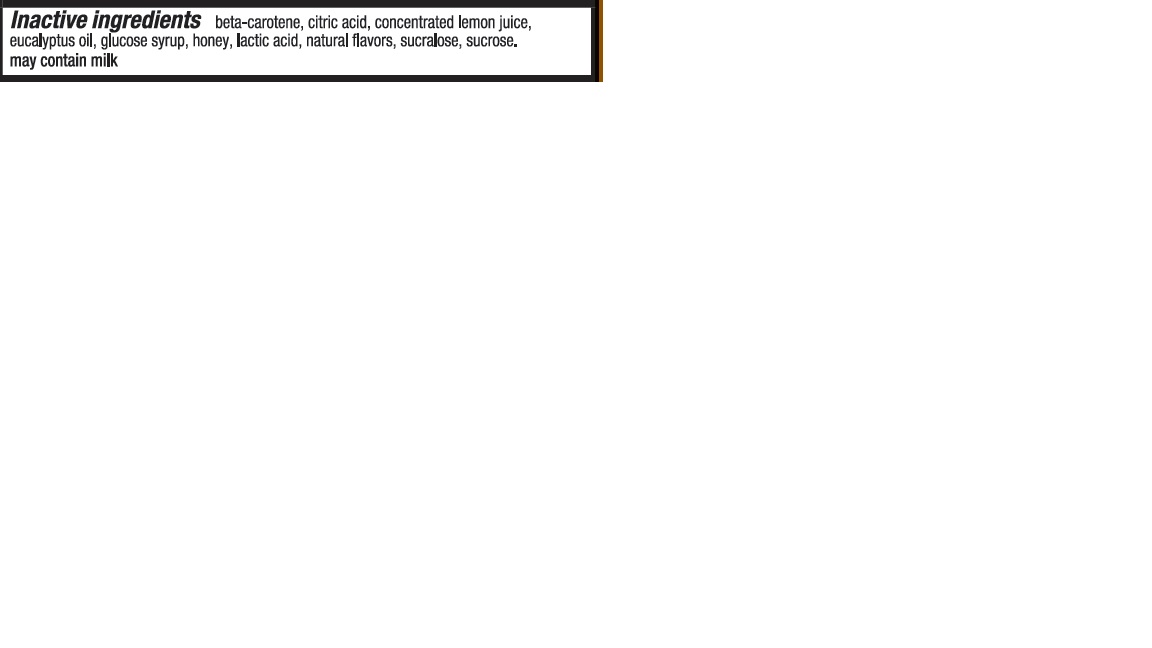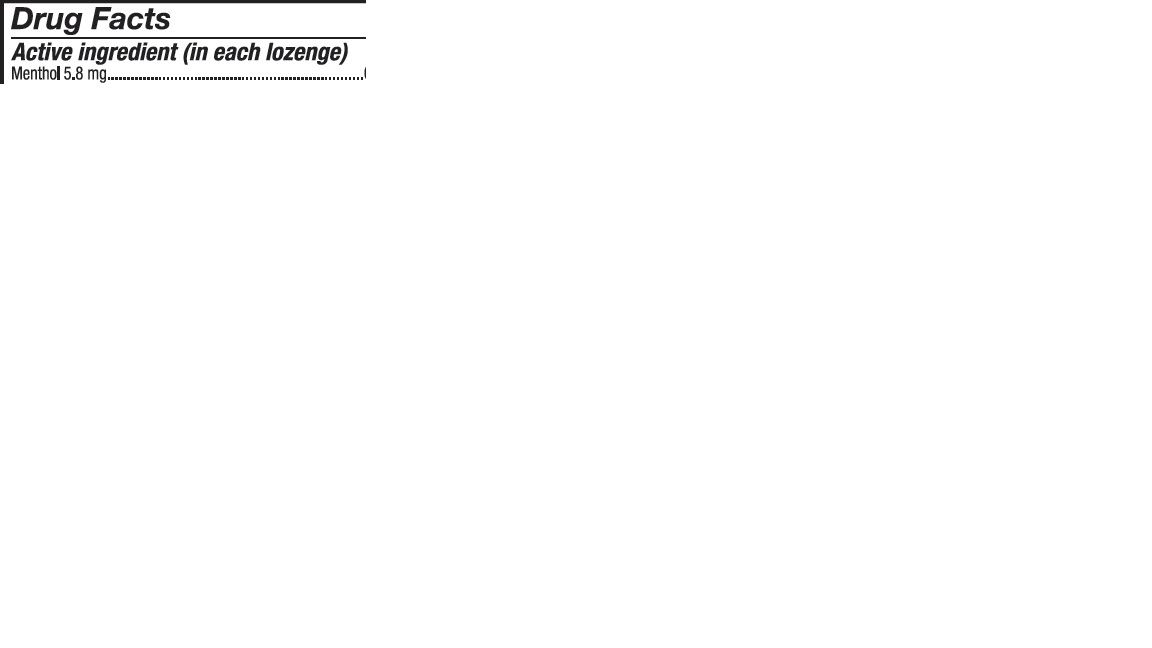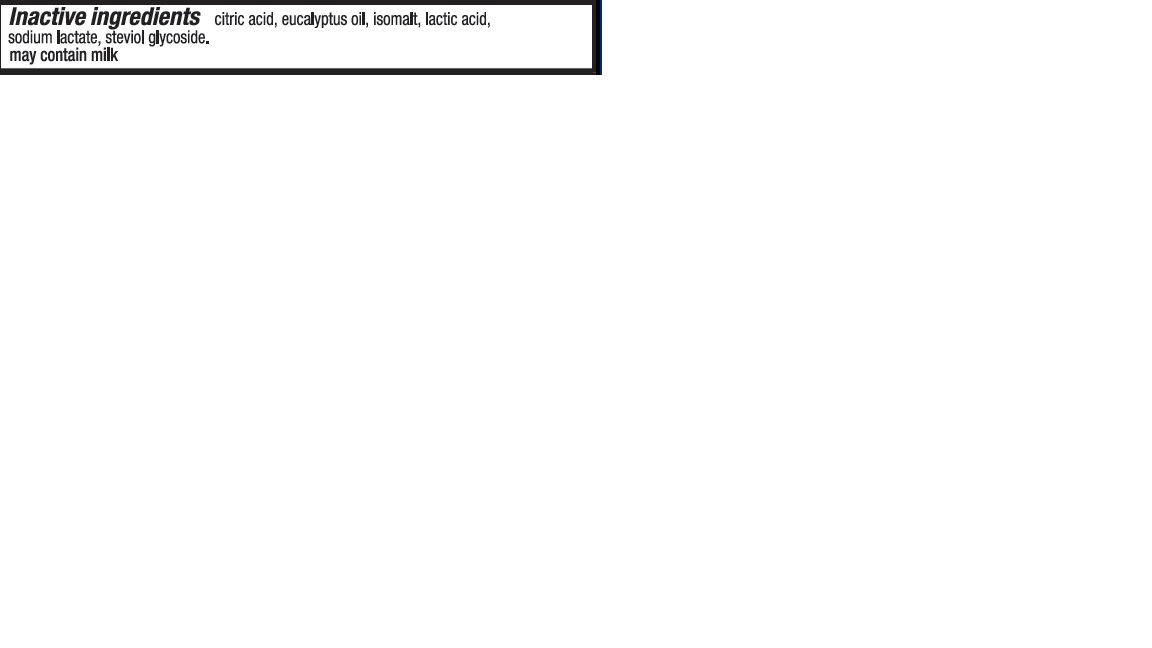 DRUG LABEL: Cough Drops Cherry with Sugar
NDC: 71141-111 | Form: TABLET
Manufacturer: Lidl US LLC
Category: otc | Type: HUMAN OTC DRUG LABEL
Date: 20241105

ACTIVE INGREDIENTS: MENTHOL 5.8 mg/5.8 mg
INACTIVE INGREDIENTS: ALCOHOL; CALCIUM CHLORIDE; EUCALYPTUS OIL; BENZYL ALCOHOL; 1,2-PROPANEDIOL, 1-BENZOATE; LACTIC ACID, UNSPECIFIED FORM; SUCROSE; CORN SYRUP; WATER; TRIACETIN; SUCRALOSE; CITRIC ACID MONOHYDRATE; COCHINEAL; MALTODEXTRIN; SODIUM CITRATE; ACETIC ACID; GELATIN

Cough Drops Honey Lemon

Tray content:

4 Menthol bags

4 Cherry bags

4 Honey Lemon bags

Cough Drops Honey Lemon

Purpose

Cough Suppressant/ Oral Anesthetic